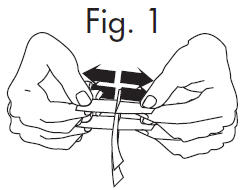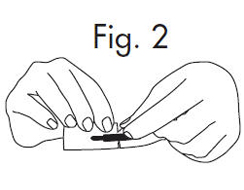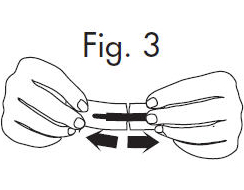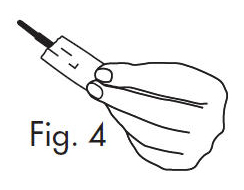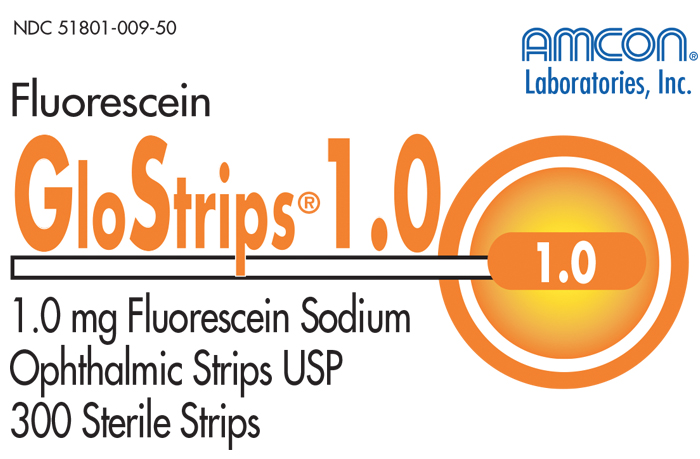 DRUG LABEL: GloStrips 
NDC: 51801-009 | Form: STRIP
Manufacturer: Nomax Inc.
Category: prescription | Type: HUMAN PRESCRIPTION DRUG LABEL
Date: 20191223

ACTIVE INGREDIENTS: Fluorescein Sodium 1 mg/1 1

GloStrips® 1.0

Fluorescein Sodium Ophthalmic Strips U.S.P. diagnostic agent is for professional use only

Each strip is impregnated with 1.0 mg of fluorescein sodium USP.

INDICATIONS

For staining the anterior segment of the eye in disclosing corneal injury, in applanation tonometry and when fitting contact lenses.

DIRECTIONS FOR USE

To ensure full fluorescence and patient comfort, the GloStrip® impregnated tip should be moistened with one or two drops of sterile, isotonic saline or irrigating solution before application.

Touch conjunctiva or fornix as required with moistened tip. It is recommended that the patient blink several times after application.

NOTE: The contents may not be sterile if the individual strip package has been damaged or previously opened. This product is intended for external use only. Keep out of reach of children. Store below 30°C.

HOW SUPPLIED

Carton containing 100 or 300 sterile strips.

Nomax, Inc. • St. Louis, MO 63123 USA

Rev. 07/13
MSN 015-244

INSTRUCTIONS FOR OPENING STERILE GLOSTRIPS®

1.Grasp free tab ends of wrapping and slowly pull apart. When the white paper handle becomes visible, remove the GloStrip® from the envelope.

An Alternate Method of Opening

1.Grasp envelope firmly with two hands as shown in Fig. 2 below. Tear the envelope from both its edges to the strip handle.

2.

Hold the handle end of the GloStrip® with the left hand and the paper envelope without holding the tip with the right hand. See Fig. 3

3.

Separate the envelope at the tear, exposing the GloStrip® tip. See Fig. 4

PRINCIPAL DISPLAY PANEL - 300 Strip Carton

NDC 51801-009-50

AMCON®
Laboratories, Inc.

Fluorescein
GloStrips®1.0

1.0

1.0 mg Fluorescein Sodium
Ophthalmic Strips USP
300 Sterile Strips